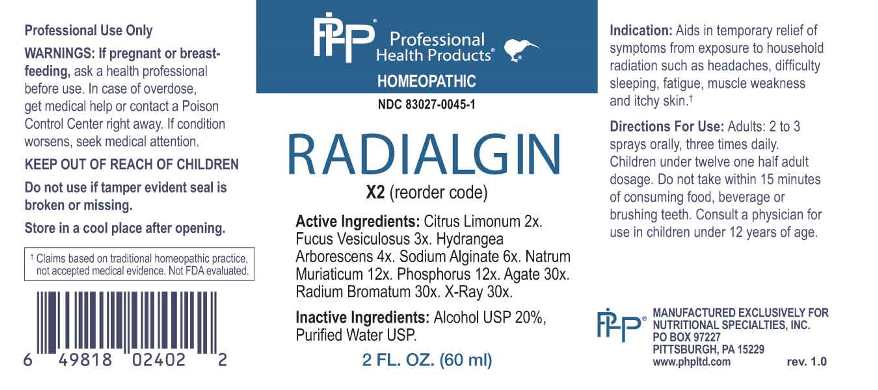 DRUG LABEL: Radialgin
NDC: 83027-0045 | Form: SPRAY
Manufacturer: Nutritional Specialties, Inc.
Category: homeopathic | Type: HUMAN OTC DRUG LABEL
Date: 20230412

ACTIVE INGREDIENTS: LEMON JUICE 2 [hp_X]/1 mL; FUCUS VESICULOSUS 3 [hp_X]/1 mL; HYDRANGEA ARBORESCENS ROOT 4 [hp_X]/1 mL; SODIUM ALGINATE 16 [hp_X]/1 mL; SODIUM CHLORIDE 12 [hp_X]/1 mL; PHOSPHORUS 12 [hp_X]/1 mL; SILICON DIOXIDE 30 [hp_X]/1 mL; RADIUM BROMIDE 30 [hp_X]/1 mL; ALCOHOL, X-RAY EXPOSED (1000 RAD) 30 [hp_X]/1 mL
INACTIVE INGREDIENTS: WATER; ALCOHOL

DRUG FACTS:

ACTIVE INGREDIENTS:

Citrus Limonum 2X, Fucus Vesiculosus 3X, Hydrangea Arborescens 4X, Sodium Alginate 6X, Natrum Muriaticum 12X, Phosphorus 12X, Agate 30X, Radium Bromatum 30X, X-Ray 30X.

PURPOSE:

Aids in temporary relief of symptoms from exposure to household radiation such as headaches, difficulty sleeping, fatigue, muscle weakness and itchy skin.†

†Claims based on traditional homeopathic practice, not accepted medical evidence. Not FDA evaluated.

WARNINGS:

Professional Use Only

If pregnant or breast-feeding, ask a health professional before use.

In case of overdose, get medical help or contact a Poison Control Center right away.

If condition worsens, seek medical attention.

KEEP OUT OF REACH OF CHILDREN

Do not use if tamper evident seal is broken or missing.

Store in a cool place after opening

KEEP OUT OF REACH OF CHILDREN:

In case of overdose, get medical help or contact a Poison Control Center right away.

DIRECTIONS:

Adults: 2 to 3 sprays orally, three times daily. Children under twelve one half adult dosage. Do not take within 15 minutes of consuming food, beverage or brushing teeth. Consult a physician for use in children under 12 years of age.

INDICATIONS:

Aids in temporary relief of symptoms from exposure to household radiation such as headaches, difficulty sleeping, fatigue, muscle weakness and itchy skin.†

†Claims based on traditional homeopathic practice, not accepted medical evidence. Not FDA evaluated.

INACTIVE INGREDIENTS:

Alcohol USP 20%, Purified Water USP.

QUESTIONS:

MANUFACTURED EXCLUSIVELY FOR

NUTRITIONAL SPECIALTIES, INC.

PO BOX 97227

PITTSBURG, PA 15229

www.phpltd.com

PACKAGE LABEL DISPLAY:

Professional

Health Products

HOMEOPATHIC

NDC 83027-0045-1

RADIALGIN

2 FL. OZ (60 ml)